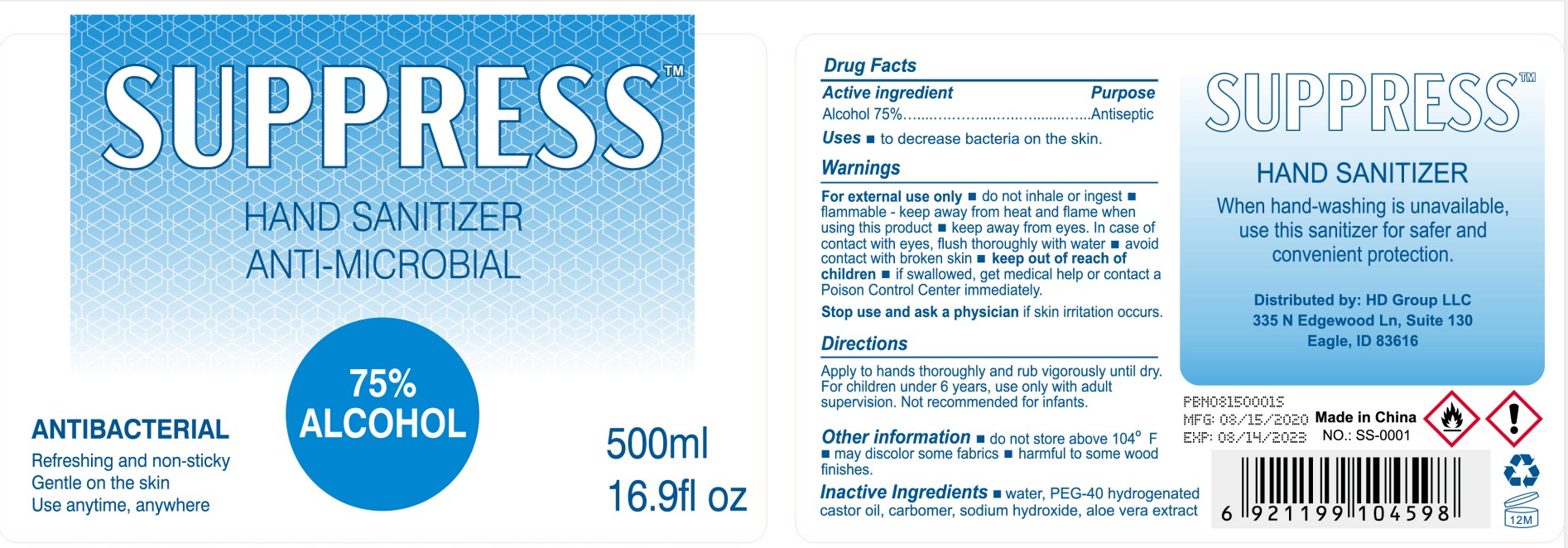 DRUG LABEL: Suppress Hand Sanitizer
NDC: 74913-610 | Form: GEL
Manufacturer: SHANTOU S.E.Z BAOJIE INDUSTRY CO., LTD
Category: otc | Type: HUMAN OTC DRUG LABEL
Date: 20200807

ACTIVE INGREDIENTS: ALCOHOL 75 mL/100 mL
INACTIVE INGREDIENTS: ALOE VERA LEAF 0.05 mL/100 mL; SODIUM HYDROXIDE 0.12 mL/100 mL; PEG-40 CASTOR OIL 0.5 mL/100 mL; CARBOMER 940 0.3 mL/100 mL; WATER 24.03 mL/100 mL

Suppress Hand Sanitizer

Active Ingredient(s)

Alcohol 75% v/v. Purpose: Antiseptic

Purpose

Antiseptic, Hand Sanitizer

Use

To decrease bacteria and other microbes

Warnings

For external use only. Flammable. Keep away from heat or flame

Do not use

- in children less than 2 months of age
- on open skin wounds

When using this product keep out of eyes, ears, and mouth. In case of contact with eyes, rinse eyes thoroughly with water.

Stop use and ask a physician if skin irritation occurs.

Keep out of reach of children. If swallowed, get medical help or contact a Poison Control Center right away.

Directions

Apply to hands thoroughly and rub vigorously until dry
For children under 6 years, use only with adult
supervision. Not recommended for infants.

Other information

do not store above 104° F
■ may discolor some fabrics ■ harmful to some wood
finishes.

Inactive ingredients

Water,Peg-40 hydrogenated, Castor oil, Carbomer,Sodium hydroxide, aloe vera extract

DESCRIPTION

Distributed by: HD Group LLC 335 N Edgewood Ln, Suite 130 Eagle, ID 83616